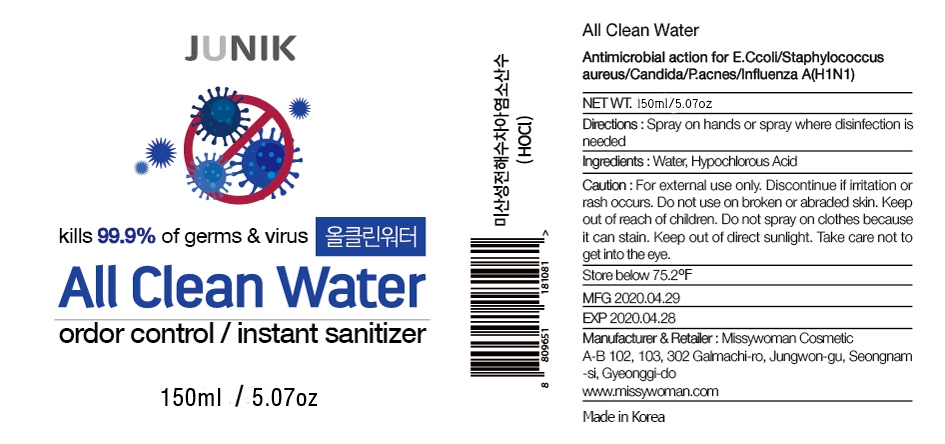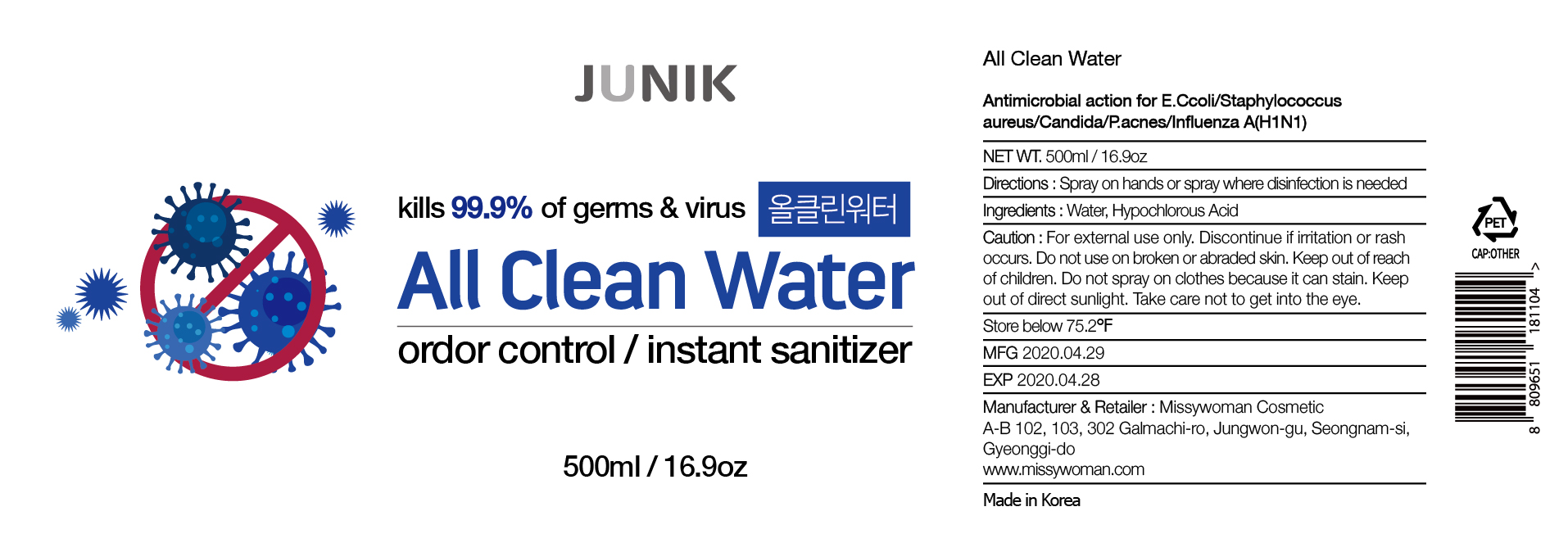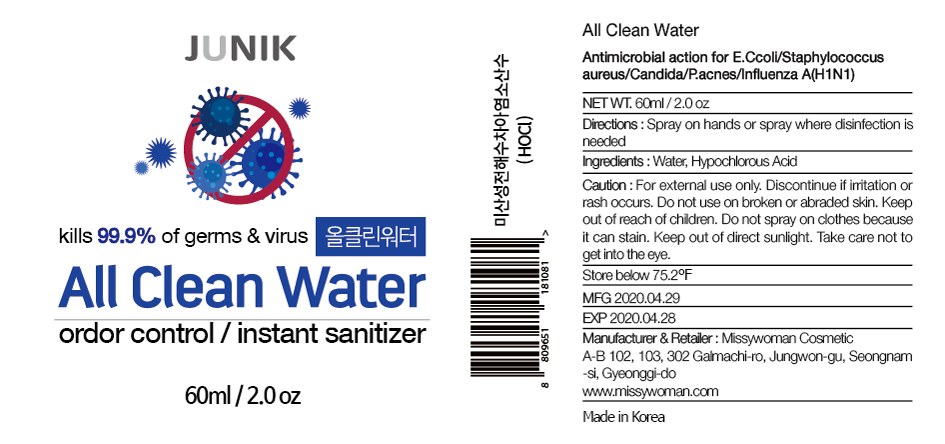 DRUG LABEL: All Clean Water
NDC: 79186-301 | Form: LIQUID
Manufacturer: MISSIWOMAN COSMETIC
Category: otc | Type: HUMAN OTC DRUG LABEL
Date: 20211216

ACTIVE INGREDIENTS: HYPOCHLOROUS ACID 0.07 g/100 mL
INACTIVE INGREDIENTS: WATER 99.93 mL/100 mL

Sanitizer

inactive ingredient

Water

Active Ingredients

Hypochlorous Acid

Direction

Spray on hands or spray where disinfection is needed

Do not use

For external use only. Discontinue if irritation or rash occurs.

Do not use on broken or abraded skin.

Use

Hand sanitizer to help reduce bacteria that potentially can cause disease.
For use when soap and water are not avaliable.

Warnings

Do not spray on clothes because it can stain.

Do not use on broken or abraded skin.

Keep out of reach of children

Stop use and ask a doctor.

Take care not to get into the eye.

If swallowed contact your doctor immediately

Stop use and ask a doctor.

if the following symptoms appear,Stop use and immediately consult a doctor: rash, erythema, itching, edema or any other skin irritation.

Other information

Keep out of direct sunlight.

Take care not to get into the eye. Store below 75.2℉

indication

After use, properly close the product to avoid drying out or spilling.

Take an appropriate amount on your hands and rub thoroughly to dry.

purpose

antimicrobial

LABEL

79186-301-01

79186-301-03

79186-301-02